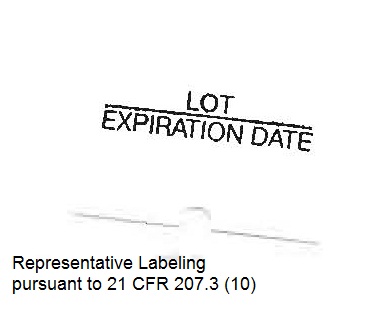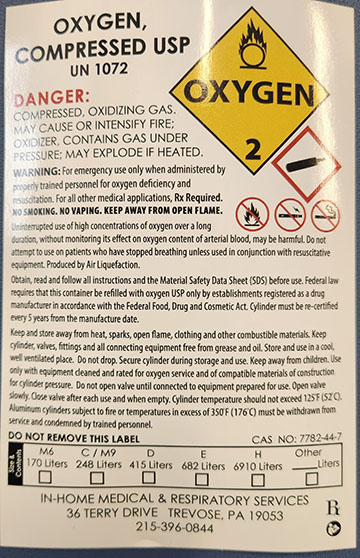 DRUG LABEL: Oxygen
NDC: 76831-001 | Form: GAS
Manufacturer: In Home Medical & Respiratory Services, Inc
Category: prescription | Type: HUMAN PRESCRIPTION DRUG LABEL
Date: 20260129

ACTIVE INGREDIENTS: OXYGEN 99 L/100 L

Oxygen

Principal for Oxygen Product

OXYGEN, COMPRESSED USP

UN 1072

DANGER:

COMPRESSED, OXIDIZING GAS.

MAY CAUSE OR INTENSIFY FIRE;

OXIDIZER, CONTAINS GAS UNDER

PRESSURE; MAY EXPLODE IF HEATED.

WARNING: For emergency use only when administered by properly trained personnel for oxygen deficiency and resuscitation. For all other medical applications, Rx Required.

NO SMOKING. NO VAPING. KEEP AWAY FROM OPEN FLAME.

Uninterrupted use of high concentrations of oxygen over a long duration, without monitoring its effect on oxygen content of arterial blood, may be harmful. Do not attempt to use on patients who have stopped breathing unless used in conjunction with resuscitative equipment. Produced by Air Liquefaction.

Obtain, read and follow all instructions and the Material Safety Data Sheet (SDS) before use. Federal law requires that this container be refilled with oxygen USP only by establishments registered as a drug manufacturer in accordance with the Federal Food, Drug and Cosmetic Act. Cylinder must be re-certified every 5 years from the manufacture date.

Keep and store away from heat, sparks, open flame, clothing and other combustible materials. Keep cylinder, valves, fittings and all connecting equipment free from grease and oil. Store and use in a cool, well ventilated place. Do not drop. Secure cylinder during storage and use. Keep away from children. Use only with equipment cleaned and rated for oxygen service and of compatible materials of construction for cylinder pressure. Do not open valve until connected to equipment prepared for use. Open valve slowly. Close valve after each use and when empty. Cylinder temperature should not exceed 125°F (52°C). Aluminum cylinders subject to fire or temperatures in excess of 350°F (176°C) must be withdrawn from service and condemned by trained personnel.

DO NOT REMOVE THIS LABEL

CAS NO: 7782-44-7

Contents:

M6 — 170 Liters ☐

C / M9 — 248 Liters ☐

D — 415 Liters ☐

E — 682 Liters ☐

H — 6910 Liters ☐

Other ____ Liters ☐

IN-HOME MEDICAL & RESPIRATORY SERVICES

36 TERRY DRIVE TREVOSE, PA 19053

215-396-0844